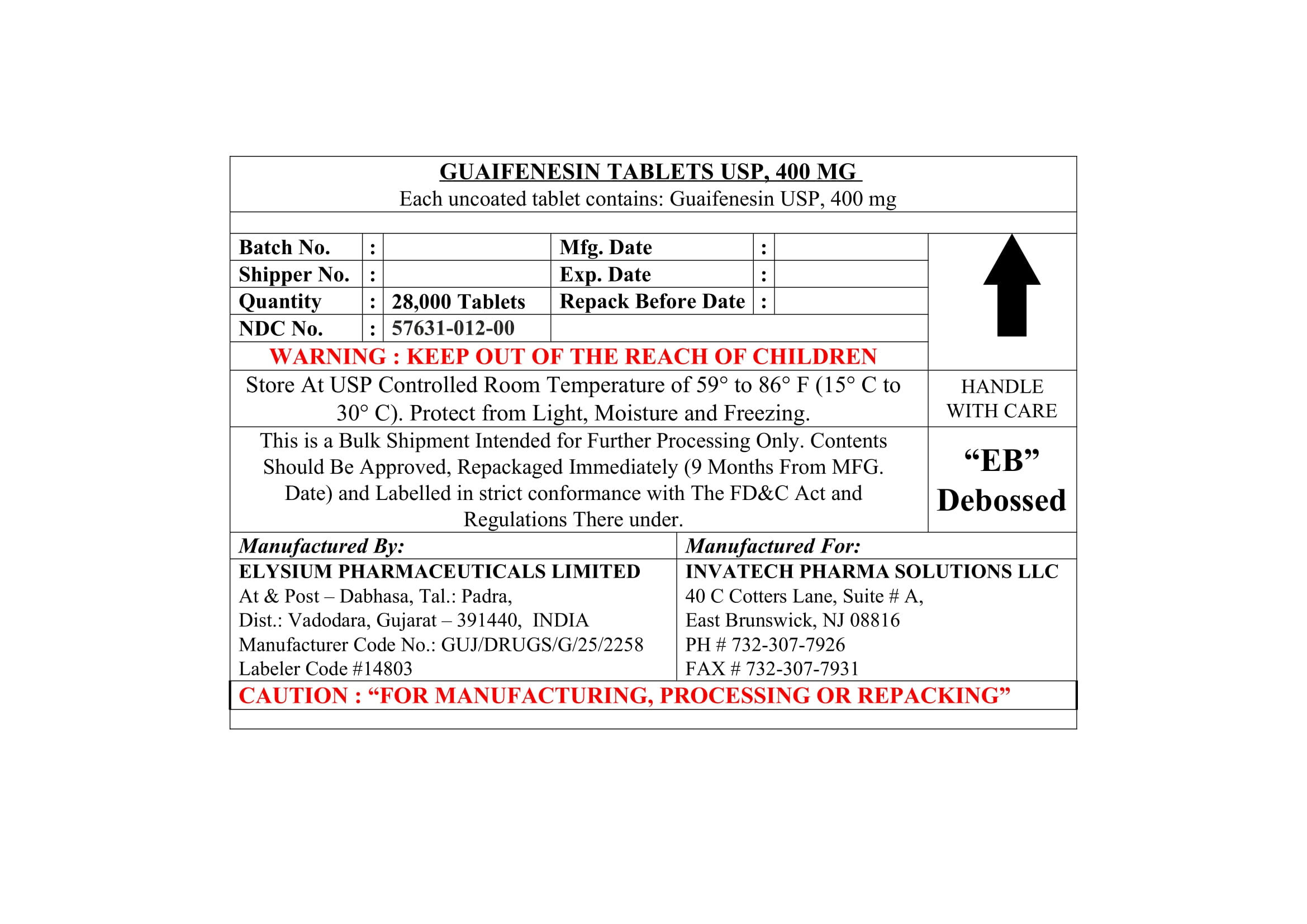 DRUG LABEL: Guaifenesin 400
NDC: 57631-012 | Form: TABLET
Manufacturer: InvaTech Pharma Solutions LLC
Category: otc | Type: HUMAN OTC DRUG LABEL
Date: 20251002

ACTIVE INGREDIENTS: GUAIFENESIN 400 mg/1 1
INACTIVE INGREDIENTS: STEARIC ACID; MAGNESIUM STEARATE; SODIUM STARCH GLYCOLATE TYPE A; POVIDONE K30; MICROCRYSTALLINE CELLULOSE; MALTODEXTRIN; SILICON DIOXIDE

Guaifenesin

INDICATIONS AND USAGE

cough, cold

INACTIVE INGREDIENT

Calcium sennosides 20% IH, Colloidal Silicon Di oxide USP/NF, Croscarmellose sodium USP/NF, Crospovidone [Kollidon] USP/NF, Dicalcium phosphate/ dibasic calcium phosphate [DIREC] USP/NF, Filmcoat AMB-51D0393632-Blue lake IH, Magnesium stearate. USP/NF, Microcrystalline cellulose (PH-102) USP/NF, Sodium lauryl sulfate USP/NF, Stearic acid powder USP/NF, Purified water

Sennosides Tablets USP, 25 mg Label